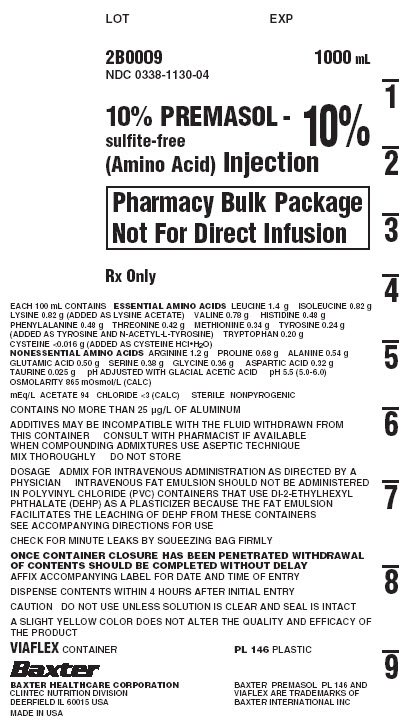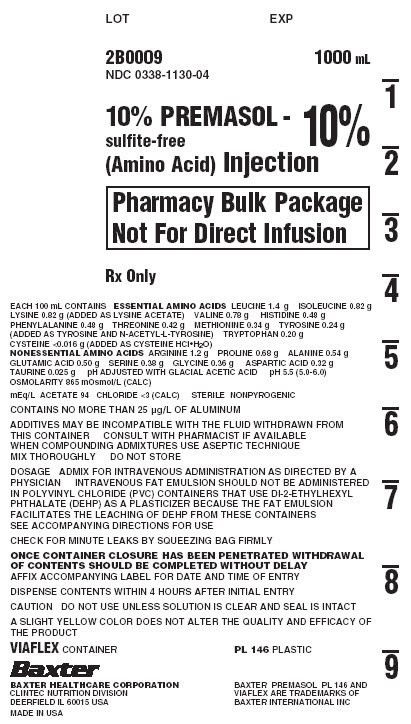 DRUG LABEL: Premasol - sulfite-free (Amino Acid)
NDC: 0338-1130 | Form: INJECTION, SOLUTION
Manufacturer: Baxter Healthcare Company
Category: prescription | Type: HUMAN PRESCRIPTION DRUG LABEL
Date: 20220804

ACTIVE INGREDIENTS: LEUCINE 1.4 g/100 mL; LYSINE ACETATE 0.82 g/100 mL; ISOLEUCINE 0.82 g/100 mL; VALINE 0.78 g/100 mL; HISTIDINE 0.48 g/100 mL; PHENYLALANINE 0.48 g/100 mL; THREONINE 0.42 g/100 mL; METHIONINE 0.34 g/100 mL; TRYPTOPHAN 0.20 g/100 mL; TYROSINE 0.24 g/100 mL; ARGININE 1.2 g/100 mL; PROLINE 0.68 g/100 mL; ALANINE 0.54 g/100 mL; GLUTAMIC ACID 0.50 g/100 mL; SERINE 0.38 g/100 mL; GLYCINE 0.36 g/100 mL; ASPARTIC ACID 0.32 g/100 mL; TAURINE 25 mg/100 mL; CYSTEINE HYDROCHLORIDE 0.016 g/100 mL
INACTIVE INGREDIENTS: ACETIC ACID; WATER; NITROGEN

PREMASOL 10% - sulfite-free (amino acids) injection
in VIAFLEX Plastic Container

Rx Only

BOXED WARNING

Pharmacy Bulk Package
Not for Direct Infusion

DESCRIPTION

PREMASOL 10% injection is a sterile, nonpyrogenic, hypertonic solutions containing crystalline amino acids provided in a Pharmacy Bulk Package. A Pharmacy Bulk Package is a container of a sterile preparation for parenteral use that contains many single doses. The contents are intended for use in a pharmacy admixture program and are restricted to the preparation of admixtures for intravenous infusion.

The VIAFLEX plastic container is fabricated from a specially formulated polyvinyl chloride (PL 146 Plastic). Exposure to temperatures above 25°C/77°F during transport and storage will lead to minor losses in moisture content. Higher temperatures lead to greater losses. It is unlikely that these minor losses will lead to clinically significant changes within the expiration period. The amount of water that can permeate from inside the container into the overwrap is insufficient to affect the solution significantly. Solutions in contact with the plastic container can leach out certain of its chemical components in very small amounts within the expiration period (e.g., di-2-ethylhexyl phthalate, DEHP, at not more than 0.2 part per million); however, the safety of the plastic has been confirmed in tests in animals according to USP biological tests for plastic containers as well as by tissue culture toxicity studies. Intravenous fat emulsion should not be administered in polyvinyl chloride (PVC) containers that use di-2-ethylhexyl phthalate (DEHP) as a plasticizer, because the fat emulsion facilitates the leaching of DEHP from these containers.

Each 100 mL contains:

Essential Amino Acids | 10%
Leucine - (CH3)2 CHCH2CH (NH2) COOH | 1.4 g
Isoleucine - CH3CH2CH (CH3) CH (NH2) COOH | 0.82 g
Lysine (added as Lysine Acetate) - H2N (CH2)4 CH (NH2) COOH | 0.82 g
Valine - (CH3)2 CHCH (NH2) COOH | 0.78 g
Histidine [Holt LE, Snyderman SE: The amino acid requirements of infants. JAMA 1961; 175(2):124-127.] - (C3H3N2) CH2CH (NH2) COOH | 0.48 g
Phenylalanine - (C6H5) CH2 CH (NH2) COOH | 0.48 g
Threonine - CH3CH (OH) CH (NH2) COOH | 0.42 g
Methionine - CH3S (CH2)2 CH (NH2) COOH | 0.34 g
Tyrosine (added as Tyrosine and N-Acetyl-L-Tyrosine) - [C6H4 (OH)] CH2CH (NH2) COOH | 0.24 g
Tryptophan - (C8H6N) CH2CH (NH2) COOH | 0.20 g
Cysteine (added as Cysteine HCl·H2O) - SHCH2 CHNH2 COOH | <0.016 g
Nonessential Amino Acids
Arginine - H2NC (NH) NH (CH2)3 CH (NH2) COOH | 1.2 g
Proline – [(CH2)3NHCH] COOH | 0.68 g
Alanine – CH3CH (NH2) COOH | 0.54 g
Glutamic Acid – HOOC (CH2)2 CH (NH2) COOH | 0.50 g
Serine - HOCH2 CH (NH2) COOH | 0.38 g
Glycine - H2NCH2COOH | 0.36 g
Aspartic Acid – HOOC CH2 CH (NH2) COOH | 0.32 g
Taurine [Rigo J, Senterre J: Is taurine essential for the neonates? Biol Neonate 1977; 32:73-76.] [Gaull G, Sturman JA, Raiha NCR: Development of mammalian sulfur metabolism: Absence of cystothionase in human fetal tissues. Pediatr Res 1972: 6:538-547.] - H2NCH2CH2SO3H | 0.025 g
pH adjusted with glacial acetic acid
pH: 5.5 (5.0-6.0)
Osmolarity (mOsmol/L) (Calc.) | 865
Total Amino Acids (grams/100 mL) (Calc.) | 10
Total Nitrogen (grams/100 mL) (Calc.) | 1.55
Acetate* - (CH3COO-) | 94 mEq/L
Chloride (Calc.) | <3 mEq/L
*Provided as acetic acid and lysine acetate.; All amino acids are added as the “L”-isomer with the exception of Glycine and Taurine, which do not have isomers.

CLINICAL PHARMACOLOGY

PREMASOL 10% injection provides a mixture of essential and nonessential amino acids as well as taurine and a soluble form of tyrosine, N-Acetyl-L-Tyrosine (NAT). This amino acid composition has been specifically formulated to provide a well tolerated nitrogen source for nutritional support and therapy for infants and young children. When administered in conjunction with cysteine hydrochloride, 10% Amino Acid Injections result in the normalization of the plasma amino acid concentrations to a profile consistent with that of a breast-fed infant.

The rationale for a 10% amino acids injection is based on the observation of inadequate levels of essential amino acids in the plasma of infants receiving total parenteral nutrition (TPN) using conventional amino acid solutions. These formulas were developed through the application of specific pharmacokinetic multiple regression analysis relating amino acid intake to the resulting plasma amino acid concentrations.

Clinical studies in infants and young children who required TPN therapy showed that infusion of a 10% amino acids injection with a cysteine hydrochloride admixture resulted in a normalization of the plasma amino acid concentrations. In addition, weight gains, nitrogen balance, and serum protein concentrations were consistent with an improving nutritional status.

When infused with hypertonic dextrose as a calorie source, supplemented with cysteine hydrochloride, electrolytes, vitamins, and minerals, PREMASOL 10% injection provides total parenteral nutrition in infants and young children, with the exception of essential fatty acids.

It is thought that the acetate from lysine acetate and acetic acid, under the conditions of parenteral nutrition, does not impact net acid-base balance when renal and respiratory functions are normal. Clinical evidence seems to support this thinking; however, confirmatory experimental evidence is not available.

The amount of chloride present in PREMASOL 10% injection is not of clinical significance. The addition of cysteine hydrochloride will contribute to the chloride load.

The electrolyte content of any additives that are introduced should be carefully considered and included in total input computations.

INDICATIONS AND USAGE

PREMASOL 10% injection is indicated for the nutritional support of infants (including those of low birth weight) and young children requiring TPN via either central or peripheral infusion routes. Parenteral nutrition with PREMASOL 10% injection is indicated to prevent nitrogen and weight loss or treat negative nitrogen balance in infants and young children where: (1) the alimentary tract, by the oral, gastrostomy, or jejunostomy route, cannot or should not be used, or adequate protein intake is not feasible by these routes; (2) gastrointestinal absorption of protein is impaired; or (3) protein requirements are substantially increased as with extensive burns. Dosage, route of administration, and concomitant infusion of non-protein calories are dependent on various factors, such as nutritional and metabolic status of the patient, anticipated duration of parenteral nutritional support, and vein tolerance (see DOSAGE AND ADMINISTRATION).

Central Venous Nutrition

Central venous infusion should be considered when amino acid solutions are to be admixed with hypertonic dextrose to promote protein synthesis in hypercatabolic or severely depleted infants, or those requiring long-term parenteral nutrition.

Peripheral Parenteral Nutrition

For moderately catabolic or depleted patients in whom the central venous route is not indicated, diluted amino acid solutions mixed with 5-10% dextrose solutions may be infused by peripheral vein, supplemented, if desired, with fat emulsion.

CONTRAINDICATIONS

PREMASOL 10% injection is contraindicated in patients with untreated anuria, hepatic coma, inborn errors of amino acid metabolism, including those involving branched chain amino acid metabolism such as maple syrup urine disease and isovaleric acidemia, or hypersensitivity to one or more amino acids present in the solution.

WARNINGS

This injection is for compounding only, not for direct infusion.

Safe, effective use of parenteral nutrition requires a knowledge of nutrition as well as clinical expertise in recognition and treatment of the complications which can occur. Frequent evaluation and laboratory determinations are necessary for proper monitoring of parenteral nutrition. Studies should include blood sugar, serum proteins, kidney and liver function tests, electrolytes, hemogram, carbon dioxide content, serum osmolalities, blood cultures, and blood ammonia levels.

Administration of amino acids in the presence of impaired renal function or gastrointestinal bleeding may augment an already elevated blood urea nitrogen. Patients with azotemia from any cause should not be infused with amino acids without regard to total nitrogen intake.

Administration of intravenous solutions can cause fluid and/or solute overload resulting in dilution of serum electrolyte concentrations, overhydration, congested states, or pulmonary edema. The risk of dilutional states is inversely proportional to the electrolyte concentrations of the solutions. The risk of solute overload causing congested states with peripheral and pulmonary edema is directly proportional to the electrolyte concentrations of the solutions.

Administration of amino acid solutions to a patient with hepatic insufficiency may result in plasma amino acid imbalances, hyperammonemia, prerenal azotemia, stupor and coma.

Hyperammonemia is of special significance in infants as its occurrence in the syndrome caused by genetic metabolic defects is sometimes associated, although not necessarily in a causal relationship, with mental retardation. This reaction appears to be dose related and is more likely to develop during prolonged therapy. It is essential that blood ammonia be measured frequently in infants. The mechanisms of this reaction are not clearly defined but may involve genetic defects and immature or subclinically impaired liver function.

Conservative doses of amino acids should be given, dictated by the nutritional status of the patient. Should symptoms of hyperammonemia develop, amino acid administration should be discontinued and patient's clinical status reevaluated.

WARNING: This product contains aluminum that may be toxic. Aluminum may reach toxic levels with prolonged parenteral administration if kidney function is impaired. Premature neonates are particularly at risk because their kidneys are immature, and they require large amounts of calcium and phosphate solutions, which contain aluminum.

Research indicates that patients with impaired kidney function, including premature neonates, who receive parenteral levels of aluminum at greater than 4 to 5 µg/kg/day accumulate aluminum at levels associated with central nervous system and bone toxicity. Tissue loading may occur at even lower rates of administration.

PRECAUTIONS

General

Clinical evaluation and periodic laboratory determinations are necessary to monitor changes in fluid balance, electrolyte concentrations, and acid-base balance during prolonged parenteral therapy or whenever the condition of the patient warrants such evaluation. Significant deviations from normal concentrations may require the use of additional electrolyte supplements.

Strongly hypertonic nutrient solutions should be administered via an intravenous catheter placed in a central vein, preferably the superior vena cava.

Care should be taken to avoid circulatory overload, particularly in patients with cardiac insufficiency.

Special care must be taken when giving hypertonic dextrose to a diabetic or pre-diabetic patient. To prevent severe hyperglycemia in such patients, insulin may be required.

Administration of glucose at a rate exceeding the patient's utilization rate may lead to hyperglycemia, coma, and death.

Administration of amino acids without carbohydrates may result in the accumulation of ketone bodies in the blood. Correction of this ketonemia may be achieved by the administration of carbohydrates.

Peripheral administration of PREMASOL 10% injection requires appropriate dilution and provision of adequate calories. Care should be taken to assure proper placement of the needle within the lumen of the vein. The venipuncture site should be inspected frequently for signs of infiltration. If venous thrombosis or phlebitis occurs, discontinue infusions or change infusion site and initiate appropriate treatment.

Extraordinary electrolyte losses such as may occur during protracted nasogastric suction, vomiting, diarrhea, or gastrointestinal fistula drainage may necessitate additional electrolyte supplementation.

Metabolic acidosis can be prevented or readily controlled by adding a portion of the cations in the electrolyte mixture as acetate salts and in the case of hyperchloremic acidosis, by keeping the total chloride content of the infusate to a minimum. PREMASOL 10% injection contains less than 3 mEq chloride per liter.

PREMASOL 10% injection contains no added phosphorus. Patients, especially those with hypophosphatemia, may require the addition of phosphate. To prevent hypocalcemia, calcium supplementation should always accompany phosphate administration. To assure adequate intake, serum levels should be monitored frequently.

To minimize the risk of possible incompatibilities arising from mixing this solution with other additives that may be prescribed, the final infusate should be inspected for cloudiness or precipitation immediately after mixing, prior to administration, and periodically during administration.

Do not use unless solution is clear and seal is intact.

Drug product contains no more than 25 µg/L of aluminum.

Carcinogenesis, Mutagenesis, Impairment of Fertility

No in vitro or in vivo carcinogenesis, mutagenesis, or fertility studies have been conducted with PREMASOL 10% injection.

Usage in Pregnancy

Animal reproduction studies have not been conducted with PREMASOL 10% injection. It is also not known whether PREMASOL 10% injection can cause fetal harm when administered to a pregnant woman or can affect reproduction capacity.

Special Precautions for Central Venous Nutrition

Administration by central venous catheter should be used only by those familiar with this technique and its complications.

Central venous nutrition may be associated with complications which can be prevented or minimized by careful attention to all aspects of the procedure, including solution preparation, administration, and patient monitoring. It is essential that a carefully prepared protocol, based on current medical practices, be followed, preferably by an experienced team.

Although a detailed discussion of the complications is beyond the scope of this insert, the following summary lists those based on current literature.

Technical.

The placement of a central venous catheter should be regarded as a surgical procedure. One should be fully acquainted with various techniques of catheter insertion as well as recognition and treatment of complications. For details of techniques and placement sites, consult the medical literature. X-ray is the best means of verifying catheter placement. Complications known to occur from the placement of central venous catheters are pneumothorax, hemothorax, hydrothorax, artery puncture and transection, injury to the brachial plexus, malposition of the catheter, formation of arteriovenous fistula, phlebitis, thrombosis, and air and catheter embolus.

Septic.

The constant risk of sepsis is present during central venous nutrition. Since contaminated solutions and infusion catheters are potential sources of infection, it is imperative that the preparation of parenteral nutrition solutions and the placement and care of catheters be accomplished under controlled aseptic conditions.

Solutions should ideally be prepared in the hospital pharmacy in a laminar flow hood. The key factor in their preparation is careful aseptic technique to avoid inadvertent touch contamination during mixing of solutions and subsequent admixtures.

Parenteral nutrition solutions should be used promptly after mixing. Any storage should be under refrigeration and limited to a brief period of time, preferably less than 24 hours.

Consult the medical literature for a discussion of the management of sepsis during central venous nutrition. In brief, typical management includes replacing the solution being administered with a fresh container and set, and the remaining contents are cultured for bacterial or fungal contamination. If sepsis persists and another source of infection is not identified, the catheter is removed, the proximal tip cultured, and a new catheter reinserted when the fever has subsided. Non-specific, prophylactic antibiotic treatment is not recommended. Clinical experience indicates that the catheter is likely to be the prime source of infection as opposed to aseptically prepared and properly stored solutions.

Metabolic.

The following metabolic complications have been reported: metabolic acidosis, hypophosphatemia, alkalosis, hyperglycemia and glycosuria, osmotic diuresis and dehydration, rebound hypoglycemia, elevated liver enzymes, hypo- and hypervitaminosis, electrolyte imbalances, and hyperammonemia in children. Frequent clinical evaluation and laboratory determinations are necessary, especially during the first few days of venous nutrition, to prevent or minimize these complications.

ADVERSE REACTIONS

See WARNINGS and Special Precautions for Central Venous Nutrition.

Reactions reported in clinical studies as a result of infusion of the parenteral fluid were water weight gain, edema, increase in BUN, and mild acidosis.

Reactions which may occur because of the solution or the technique of administration include febrile response, infection at the site of injection, venous thrombosis or phlebitis extending from the site of injection, extravasation, and hypervolemia.

Local reaction at the infusion site, consisting of a warm sensation, erythema, phlebitis and thrombosis, have been reported with peripheral amino acid infusions, especially if other substances are also administered through the same site.

If electrolyte supplementation is required during peripheral infusion, it is recommended that additives be administered throughout the day in order to avoid possible venous irritation. Irritating additive medications may require injection at another site and should not be added directly to the amino acid infusate.

Symptoms may result from an excess or deficit of one or more of the ions present in the solution; therefore, frequent monitoring of electrolyte levels is essential.

Phosphorus deficiency may lead to impaired tissue oxygenation and acute hemolytic anemia. Relative to calcium, excessive phosphorus intake can precipitate hypocalcemia with cramps, tetany and muscular hyperexcitability.

If an adverse reaction does occur, discontinue the infusion, evaluate the patient, institute appropriate therapeutic countermeasures, and save the remainder of the fluid for examination if deemed necessary.

OVERDOSAGE

In the event of a fluid or solute overload during parenteral therapy, reevaluate the patient's condition, and institute appropriate corrective treatment.

DOSAGE AND ADMINISTRATION

The objective of nutritional management of infants and young children is the provision of sufficient amino acid and caloric support for protein synthesis and growth.

The total daily dose of PREMASOL 10% injection depends on daily protein requirements and on the patient's metabolic and clinical response. The determination of nitrogen balance and accurate daily body weights, corrected for fluid balance, are probably the best means of assessing individual protein requirements. Dosage should also be guided by the patient's fluid intake limits and glucose and nitrogen tolerances, as well as by metabolic and clinical response.

Recommendations for allowances of protein in infant nutrition have ranged from 2 to 4 grams of protein per kilogram of body weight per day (2.0 to 4.0 g/kg/day) [Suskind RM: Textbook of Pediatric Nutrition, Raven Press, New York, 1981.] . The recommended dosage of PREMASOL 10% injection is 2.0 to 2.5 grams of amino acids per kilogram of body weight per day (2.0 to 2.5 g/kg/day) for infants up to 10 kilograms. For infants and young children larger than 10 kilograms, the total dosage of amino acids should include the 20 to 25 grams/day for the first 10 kg of body weight plus 1.0 to 1.25 g/day for each kg of body weight over 10 kilograms.

Typically, PREMASOL 10% injection is admixed with 50% or 70% Dextrose Injection USP supplemented with electrolytes and vitamins and administered continuously over a 24 hour period.

Total daily fluid intake should be appropriate for the patient's age and size. A fluid dose of 125 mL per kilogram body weight per day is appropriate for most infants on TPN. Although nitrogen requirements may be higher in severely hypercatabolic or depleted patients, provision of additional nitrogen may not be possible due to fluid intake limits, nitrogen, or glucose intolerance.

Cysteine is considered to be an essential amino acid in infants and young children. An admixture of cysteine hydrochloride to the TPN solution is therefore recommended. Based on clinical studies, the recommended dosage is 1.0 mmol of L-cysteine hydrochloride monohydrate per kilogram of body weight per day.

In many patients, provision of adequate calories in the form of hypertonic dextrose may require the administration of exogenous insulin to prevent hyperglycemia and glycosuria. To prevent rebound hypoglycemia, a solution containing 5% dextrose should be administered when hypertonic dextrose solutions are abruptly discontinued.

Fat emulsion coadministration should be considered when prolonged (more than 5 days) parenteral nutrition is required in order to prevent essential fatty acid deficiency (EFAD). Serum lipids should be monitored for evidence of EFAD in patients maintained on fat free TPN.

The provision of sufficient intracellular electrolytes, principally potassium, magnesium, and phosphate, is required for optimum utilization of amino acids. In addition, sufficient quantities of the major extracellular electrolytes sodium, calcium, and chloride, must be given. In patients with hyperchloremic or other metabolic acidosis, sodium and potassium may be added as the acetate salts to provide bicarbonate precursor. The electrolyte content of PREMASOL 10% injection must be considered when calculating daily electrolyte intake. Serum electrolytes, including magnesium and phosphorus, should be monitored frequently.

Appropriate vitamins, minerals and trace elements should also be provided.

Central Venous Nutrition.

Hypertonic mixtures of amino acids and dextrose may be safely administered by continuous infusion through a central venous catheter with the tip located in the superior vena cava. Initial infusion rates should be slow, and gradually increased to the recommended 60-125 mL per kilogram of body weight per day. If administration rate should fall behind schedule, no attempt to “catch up” to planned intake should be made. In addition to meeting protein needs, the rate of administration, particularly during the first few days of therapy, is governed by the patient's glucose tolerance. Daily intake of amino acids and dextrose should be increased gradually to the maximum required dose as indicated by frequent determinations of glucose levels in blood and urine.

Peripheral Parenteral Nutrition.

For patients in whom the central venous route is not indicated and who can consume adequate calories enterally, PREMASOL 10% injection may be administered by peripheral vein with or without parenteral carbohydrate calories. Such infusates can be prepared by dilution with Sterile Water for Injection or 5% -10% Dextrose Injection to prepare isotonic or slightly hypertonic solutions for peripheral infusion. It is essential that peripheral infusion be accompanied by adequate caloric intake.

Parenteral drug products should be inspected visually for particulate matter and discoloration prior to administration, whenever solution and container permit.

A slight yellow color does not alter the quality and efficacy of the product.

PREMASOL 10% injection may be admixed with solutions which contain phosphate or which have been supplemented with phosphate. The presence of calcium and magnesium ions in an additive solution should be considered when phosphate is also present, in order to avoid precipitation.

Care must be taken to avoid incompatible admixtures. Consult with pharmacist.

Parenteral nutrition solutions should be used promptly after mixing. Any storage should be under refrigeration and limited to a brief period of time, preferably less than 24 hours.

Directions for use of VIAFLEX plastic Pharmacy Bulk Package container

To Open

Tear overpouch across top at slit and remove solution container. Discard overpouch and sachet. Visually inspect the container. If the outlet port protector is damaged, detached, or not present, discard container as solution path sterility may be impaired. Some opacity of the plastic due to moisture absorption during the sterilization process may be observed. This is normal and does not affect the solution quality or safety. The opacity will diminish gradually. Check for minute leaks by squeezing inner bag firmly. If leaks are found, discard solution as sterility may be impaired.

For compounding only, not for direct infusion.

Preparation for Admixing

1. The Pharmacy Bulk Package is to be used only in a suitable work area such as a laminar flow hood (or an equivalent clean air compounding area).
2. Suspend container from eyelet support.
3. Remove plastic protector from outlet port at bottom of container.
4. Attach solution transfer set. Refer to complete directions accompanying set. Note: The closure shall be penetrated only one time with a suitable sterile transfer device or dispensing set which allows measured dispensing of the contents.
5. VIAFLEX containers should not be written on directly since ink migration has not been investigated. Affix accompanying label for date and time of entry.
6. Once container closure has been penetrated, withdrawal of contents should be completed without delay. After initial entry, maintain contents at room temperature (25°C/77°F) and dispense within 4 hours.

Intravenous fat emulsion should not be administered in polyvinyl chloride (PVC) containers that use di-2-ethylhexyl phthalate (DEHP) as a plasticizer, because the fat emulsion facilitates the leaching of DEHP from these containers.

HOW SUPPLIED

PREMASOL 10% - sulfite-free (amino acids) injection is supplied in VIAFLEX plastic Pharmacy Bulk Package containers in the following sizes and concentrations:

 | 500 mL | 1000 mL | 2000 mL
10% | 2B0012 | 2B0009 | 2B0010
 | NDC 0338-1130-03 | NDC 0338-1130-04 | NDC 0338-1130-06

Exposure of pharmaceutical products to heat should be minimized. Avoid excessive heat. Protect from freezing. It is recommended the product be stored at room temperature (25°C/77°F). Brief exposure up to 40°C/104°F does not adversely affect the product.

Protect from light until immediately prior to use.

Do not remove container from overpouch until ready to use.

Do not use if overpouch has been previously opened or damaged.

Baxter Healthcare Corporation
Deerfield, IL 60015 USA

Printed in USA

Baxter, Premasol, and Viaflex are trademarks of Baxter International Inc.

07-19-00-3923
Rev. November 2021

PACKAGE LABEL - PRINCIPAL DISPLAY PANEL

Container Label

LOT
EXP

2B0009
NDC 0338-1130-04

1000 mL
10% PREMASOL -

sulfite-free
(Amino Acid) Injection

10%

Pharmacy Bulk Package
Not For Direct Infusion

Rx Only

Each 100 mL contains Essential Amino Acids LEUCINE 1.4 g ISOLEUCINE 0.82 g
LYSINE 0.82 g (ADDED AS LYSINE ACETATE) VALINE 0.78 g HISTIDINE 0.48 g
PHENYLALANINE 0.48 g THREONINE 0.42 g METHIONINE 0.34 g TYROSINE 0.24 g
(ADDED AS TYROSINE AND N-ACETYL-L-TYROSINE) TRYPTOPHAN 0.20 g
CYSTEINE <0.016 g (ADDED AS CYSTEINE HCl•H2O)

Nonessential Amino Acids ARGININE 1.2 g PROLINE 0.68 g ALANINE 0.54 g

GLUTAMIC ACID 0.50 g SERINE 0.38 g GLYCINE 0.36 g ASPARTIC ACID 0.32 g
TAURINE 0.025 g pH ADJUSTED WITH GLACIAL ACETIC ACID pH 5.5 (5.0-6.0)

OSMOLARITY 865 mOsmol/L (CALC)

mEq/L ACETATE 94 CHLORIDE <3 (CALC) STERILE NONPYROGENIC

CONTAINS NO MORE THAN 25 μg/L OF ALUMINUM

ADDITIVES MAY BE INCOMPATIBLE WITH TH E FLUID WITH DRAWN FROM
THIS CONTAINER CONSULT WITH PHARMACIST IF AVAILABLE
WHEN COMPOUNDING ADMIXTURES USE ASEPTIC TECHNIQUE

MIX THOROUGHLY DO NOT STORE

DOSAGE ADMIX FOR INTRAVENOUS ADMINISTRATION AS DIRECTED BY A
PHYSICIAN INTRAVENOUS FAT EMULSION SHOULD NOT BE ADMINISTERED
IN POLYVINYL CHLORIDE (PVC) CONTAINERS THAT USE DI-2-ETHYLHEXYL
PHTHALATE (DEHP) AS A PLASTICIZER BECAUSE THE FAT EMULSION
FACILITATES THE LEACHING OF DEHP FROM THESE CONTAINERS
SEE ACCOMPANYING DIRECTIONS FOR USE

CHECK FOR MINUTE LEAKS BY SQUEEZING BAG FIRMLY

ONCE CONTAINER CLOSURE HAS BEEN PENETRATED WITHDRAWAL
OF CONTENTS SHOULD BE COMPLETED WITHOUT DELAY
AFFIX ACCOMPANYING LABEL FOR DATE AND TIME OF ENTRY

DISPENSE CONTENTS WITHIN 4 HOURS AFTER INITIAL ENTRY

CAUTION DO NOT USE UNLESS SOLUTION IS CLEAR AND SEAL IS INTACT

A SLIGHT YELLOW COLOR DOES NOT ALTER THE QUALITY AND EFFICACY OF
THE PRODUCT

VIAFLEX CONTAINER

PL 146 PLASTIC

Baxter Logo
BAXTER HEALTHCARE CORPORATION
CLINTEC NUTRITION DIVISION
DEERFIELD IL 60015 USA
MADE IN USA

BAXTER PREMASOL PL 146 AND
VIAFLEX ARE TRADEMARKS OF
BAXTER INTERNATIONAL INC

-
1

-
2

-
3

-
4

-
5

-
6

-
7

-
8

-
9

Container Label

LOT
EXP

2B0009
NDC 0338-1130-04

1000 mL
10% PREMASOL -

sulfite-free
(Amino Acid) Injection

10%

Pharmacy Bulk Package
Not For Direct Infusion

Rx Only

Each 100 mL contains Essential Amino Acids LEUCINE 1.4 g ISOLEUCINE 0.82 g
LYSINE 0.82 g (ADDED AS LYSINE ACETATE) VALINE 0.78 g HISTIDINE 0.48 g
PHENYLALANINE 0.48 g THREONINE 0.42 g METHIONINE 0.34 g TYROSINE 0.24 g
(ADDED AS TYROSINE AND N-ACETYL-L-TYROSINE) TRYPTOPHAN 0.20 g
CYSTEINE <0.016 g (ADDED AS CYSTEINE HCl•H2O)

Nonessential Amino Acids ARGININE 1.2 g PROLINE 0.68 g ALANINE 0.54 g

GLUTAMIC ACID 0.50 g SERINE 0.38 g GLYCINE 0.36 g ASPARTIC ACID 0.32 g
TAURINE 0.025 g pH ADJUSTED WITH GLACIAL ACETIC ACID pH 5.5 (5.0-6.0)

OSMOLARITY 865 mOsmol/L (CALC)

mEq/L ACETATE 94 CHLORIDE <3 (CALC) STERILE NONPYROGENIC

CONTAINS NO MORE THAN 25 μg/L OF ALUMINUM

ADDITIVES MAY BE INCOMPATIBLE WITH TH E FLUID WITH DRAWN FROM
THIS CONTAINER CONSULT WITH PHARMACIST IF AVAILABLE
WHEN COMPOUNDING ADMIXTURES USE ASEPTIC TECHNIQUE

MIX THOROUGHLY DO NOT STORE

DOSAGE ADMIX FOR INTRAVENOUS ADMINISTRATION AS DIRECTED BY A
PHYSICIAN INTRAVENOUS FAT EMULSION SHOULD NOT BE ADMINISTERED
IN POLYVINYL CHLORIDE (PVC) CONTAINERS THAT USE DI-2-ETHYLHEXYL
PHTHALATE (DEHP) AS A PLASTICIZER BECAUSE THE FAT EMULSION
FACILITATES THE LEACHING OF DEHP FROM THESE CONTAINERS
SEE ACCOMPANYING DIRECTIONS FOR USE

CHECK FOR MINUTE LEAKS BY SQUEEZING BAG FIRMLY

ONCE CONTAINER CLOSURE HAS BEEN PENETRATED WITHDRAWAL
OF CONTENTS SHOULD BE COMPLETED WITHOUT DELAY
AFFIX ACCOMPANYING LABEL FOR DATE AND TIME OF ENTRY

DISPENSE CONTENTS WITHIN 4 HOURS AFTER INITIAL ENTRY

CAUTION DO NOT USE UNLESS SOLUTION IS CLEAR AND SEAL IS INTACT

A SLIGHT YELLOW COLOR DOES NOT ALTER THE QUALITY AND EFFICACY OF
THE PRODUCT

VIAFLEX CONTAINER

PL 146 PLASTIC

Baxter Logo
BAXTER HEALTHCARE CORPORATION
CLINTEC NUTRITION DIVISION
DEERFIELD IL 60015 USA
MADE IN USA

BAXTER PREMASOL PL 146 AND
VIAFLEX ARE TRADEMARKS OF
BAXTER INTERNATIONAL INC

-
1

-
2

-
3

-
4

-
5

-
6

-
7

-
8

-
9